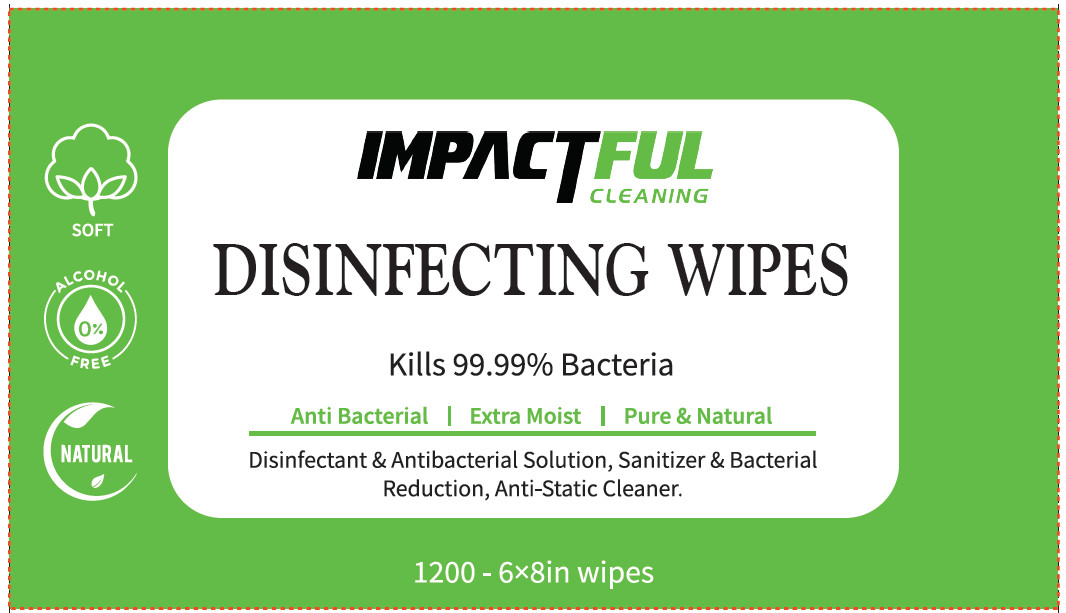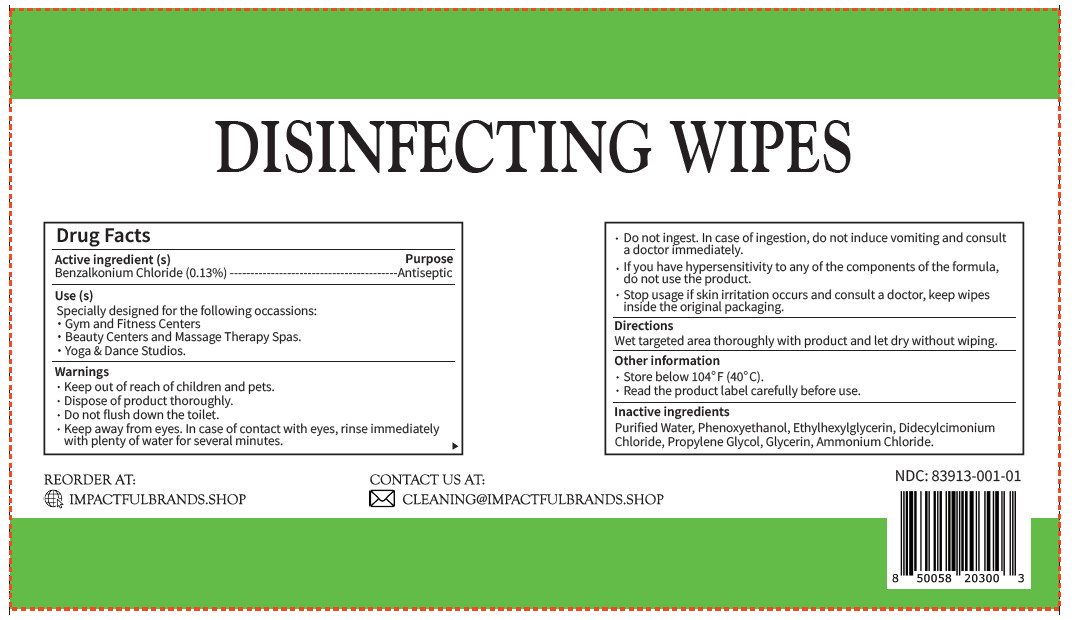 DRUG LABEL: IMPACTFUL CLEANING DISINFECTING WIPES
NDC: 83913-001 | Form: CLOTH
Manufacturer: IMPACTFUL BRANDS LLC
Category: otc | Type: HUMAN OTC DRUG LABEL
Date: 20240325

ACTIVE INGREDIENTS: BENZALKONIUM CHLORIDE 0.13 g/100 g
INACTIVE INGREDIENTS: WATER; PHENOXYETHANOL; ETHYLHEXYLGLYCERIN; PROPYLENE GLYCOL; DIDECYLDIMONIUM CHLORIDE; GLYCERIN; AMMONIUM CHLORIDE

83913-001 IMPACTFUL CLEANING DISINFECTING WIPES

Active ingredient (s)
Benzalkonium Chloride (0.13%)

Purpose

Antiseptic

INDICATIONS AND USAGE

Use (s)
Specially designed for the following occassions:
· Gym and Fitness Centers
· Beauty Centers and Massage Therapy Spas.
· Yoga & Dance Studios.

Warnings

· Keep out of reach of children and pets.

· Dispose of product thoroughly.

· Do not flush down the toilet.

· Keep away from eyes. In case of contact with eyes, rinse immediately with plenty of water for several minutes.

· Do not ingest. In case of ingestion, do not induce vomiting and consult a doctor immediately.

· If you have hypersensitivity to any of the components of the formula, do not use the product.

· Stop usage if skin irritation occurs and consult a doctor, keep wipes inside the original packaging.

· Keep out of reach of children and pets.

STOP USE

· Stop usage if skin irritation occurs and consult a doctor, keep wipes inside the original packaging.

Directions
Wet targeted area thoroughly with product and let dry without wiping.

Other information

· Store below 104℉ (40°C).

· Read the product label carefully before use.

Inactive ingredients

Purified Water, Phenoxyethanol, Ethylhexylglycerin, Didecylcimonium

Chloride, Propylene Glycol, Glycerin, Ammonium Chloride.

PACKAGE LABEL

NDC: 83913-001-01